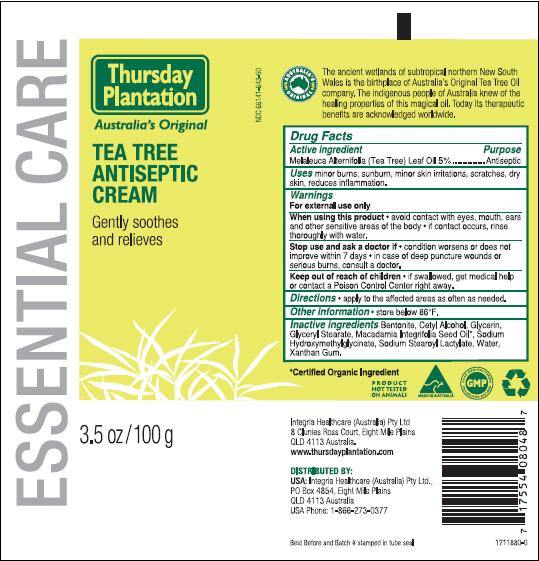 DRUG LABEL: Thursday Plantation
NDC: 66141-643 | Form: CREAM
Manufacturer: Integria Healthcare Ballina
Category: otc | Type: HUMAN OTC DRUG LABEL
Date: 20100208

ACTIVE INGREDIENTS: AUSTRALIAN TEA TREE OIL 5 g/100 g

Active Ingredient: melaleuca Alternifolia (Tea Tree) Leaf Oil 5%

INDICATIONS AND USAGE

Uses: minor burns, sunburn, minor skin irritations, scratches, dry skin, reduces inflammation

Warnings:

For external use only

When using this product - avoid contact with eyes, mouth, ears and other sensitive areas of the body - if contact occurs, rinse thoroughly with water.

Stop use and ask a doctor if - condition worsens or does not improve within 7 days - in case of deep puncture wounds or serious burns, consult a doctor.

Keep out of reach of children - if swallowed, get medical help or contact a Poison Control Center right away.

DOSAGE AND ADMINISTRATION

Directions - apply to the affected areas as often as needed.

Other Information - store below 86 degrees F.

Integria Healthcare Australia Pty Ltd
8 Clunies Ross Court, Eight Mile Plains
QLD 4113 Australia
www.thursdayplantation.com

Distributed by:
USA: Integria Healthcare (Australia) Pty Ltd.
PO Box 4854, Eight Mile Plains
QLD 4113 Australia
USA Phone: 1-866-273-0377

INACTIVE INGREDIENT

Inactive Ingredients: Bentonite, Cetyl Alcohol, Glycerin, Glyceryl Stearate, Macadamia Integrifolia Seed Oil, Sodium Hydroxymethylglycinate, Sodium Stearoyl Lactylate, Water, Xantham Gum.

PACKAGE LABEL

Thursday Plantation

Tea Tree Antiseptic Cream

Gently soothes and relieves